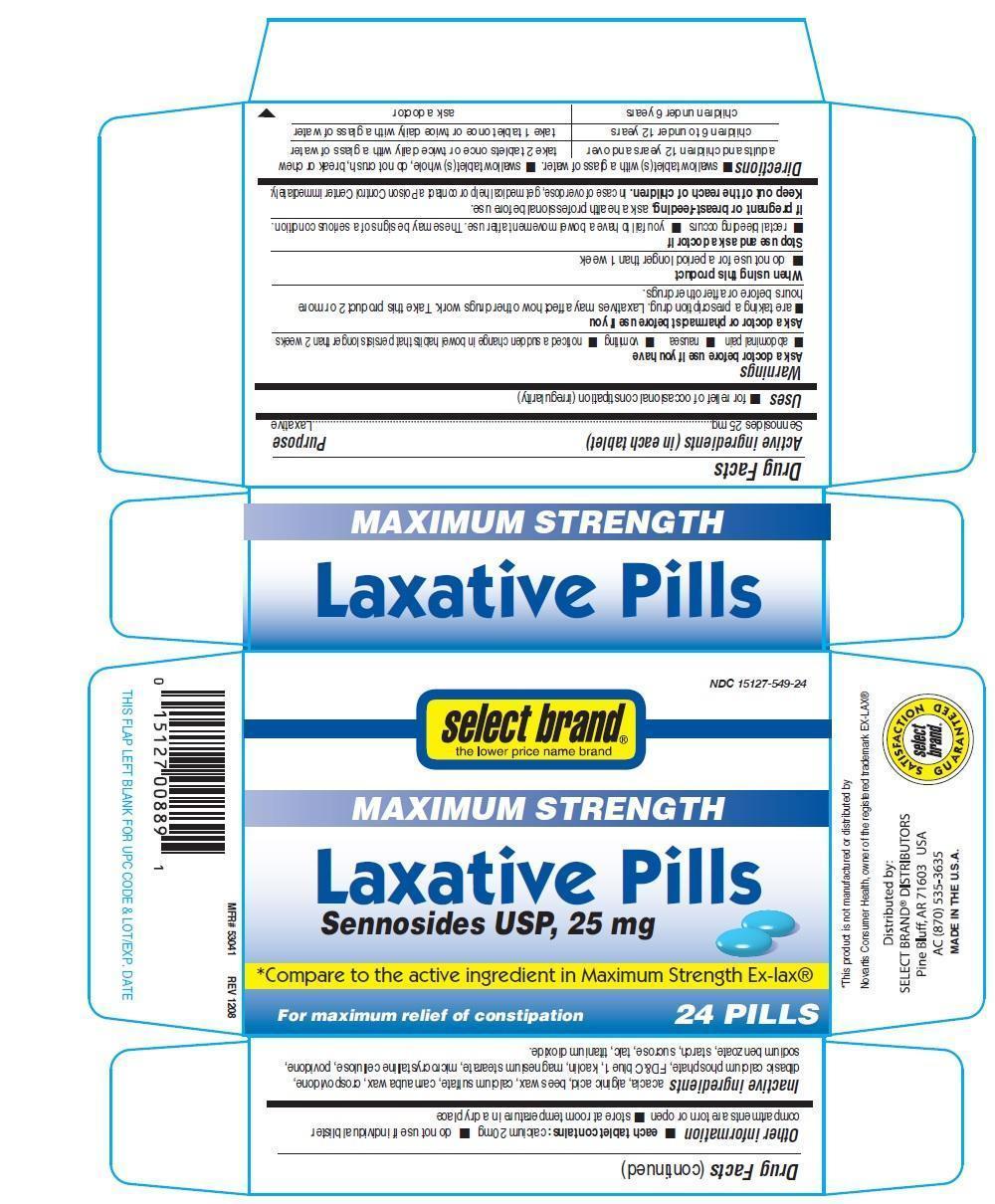 DRUG LABEL: Laxative Pills
NDC: 15127-549 | Form: PILL
Manufacturer: Select Brand
Category: otc | Type: HUMAN OTC DRUG LABEL
Date: 20140905

ACTIVE INGREDIENTS: SENNOSIDES 25 mg/1 1
INACTIVE INGREDIENTS: ACACIA; ALGINIC ACID; YELLOW WAX; CALCIUM SULFATE; CARNAUBA WAX; CROSPOVIDONE; ANHYDROUS DIBASIC CALCIUM PHOSPHATE; FD&C BLUE NO. 1; KAOLIN; MAGNESIUM STEARATE; CELLULOSE, MICROCRYSTALLINE; POVIDONE; SODIUM BENZOATE; STARCH, CORN; SUCROSE; TALC; TITANIUM DIOXIDE

Select Brand Maximum strength Laxative Pills

Active ingredient (in each tablet)

Sennosides 25 mg

Purpose

Laxative

Uses

- for relief of occasional costipation (irregularity)

Warnings

Ask a doctor before use if you have

- abdominal pain
- nausea
- vomiting
- noticed a sudeen change in bowel habits that persists longer than 2 weeks

Ask a doctor or pharmacist before use if you

- are taking a prescription drug. Laxatives may affect how other drugs work. Take this produtc 2 or more hours before or after other drugs.

When using this product

- do not use for a period longer than 1 week

Stop use and ask a doctor if

- rectal bleeding occurs
- you fail to have a bowel movement after use. These may be signs of a serious condition.

If Pregnant or breast feeding,

ask a health professional before use.

Keep out of the reach of children. In case of overdose, get medical help or contact a poison control center immediately

Directions

- Swallow tablets(s) with a glass of water
- swallow tablets(s) whole, do not crush, break or chew

adults and children 12 years and over | take 2 tablets once or twice daily with a glass of water
children 6 to under 12 years | take 1 tablet once or twice daily with a glass of water
children under 6 years | ask a doctor

Other information

- each tablet contains: calcium 20mg
- do not use if individual blister compartments are torn or opem
- store at room temperature in a dry place

Inactive ingredients

acacia, alginic acid, bees wax, calcium sulfate, carnauba wax, crospovidone, dibasic calcium phosphate, FD&C blue 1, Kaolin, magnesium stearate, microcrystalline cellulose, povidone, sodium benzoate, starch, sucrose, talc, titanium dioxide

PDP

Select Brand

Maximum Strength

Laxative Pills

Sennosides USP, 25 mg

Compare to the active ingredient in Maximum strength Ex-Lax

For maximum relief of constipation

24 Pills